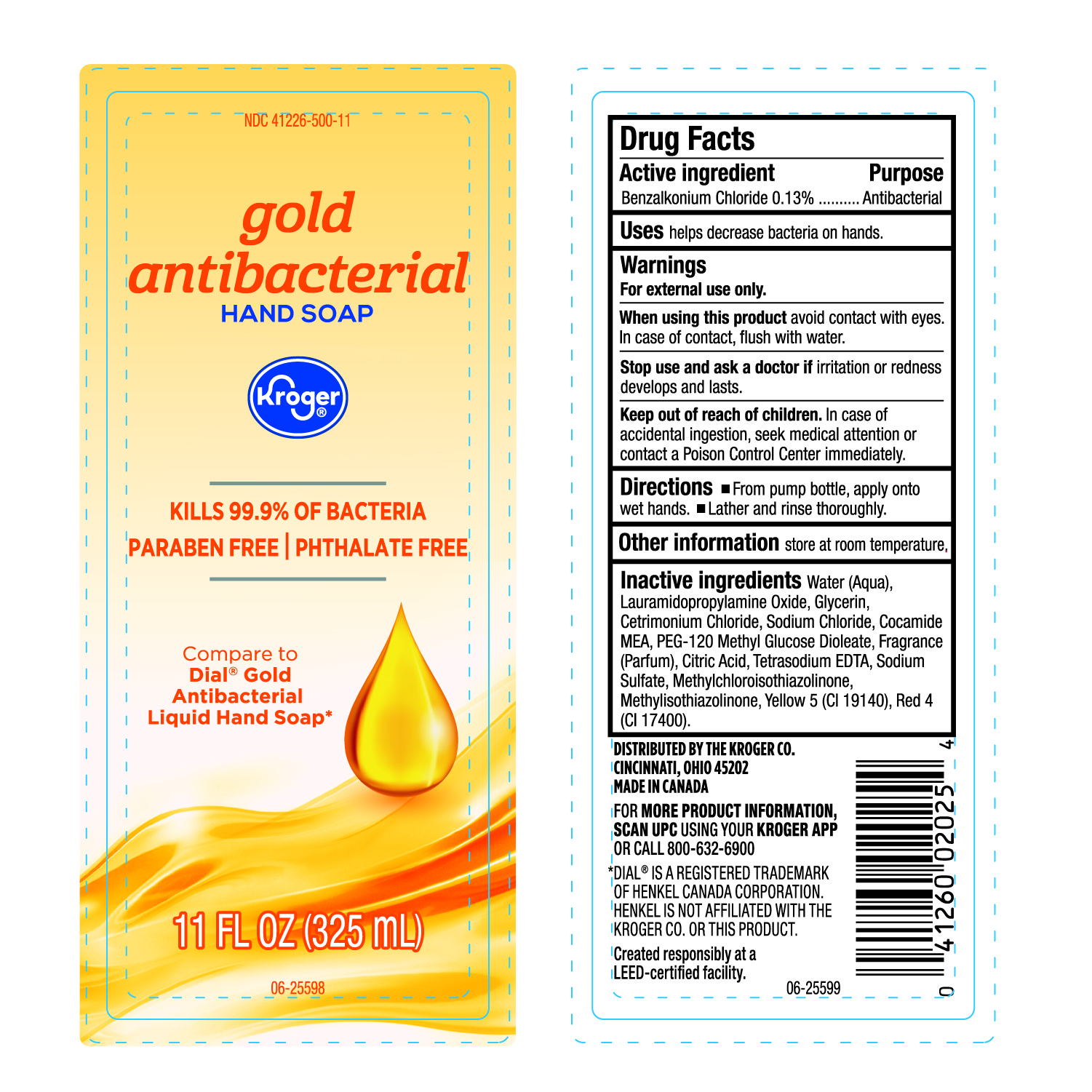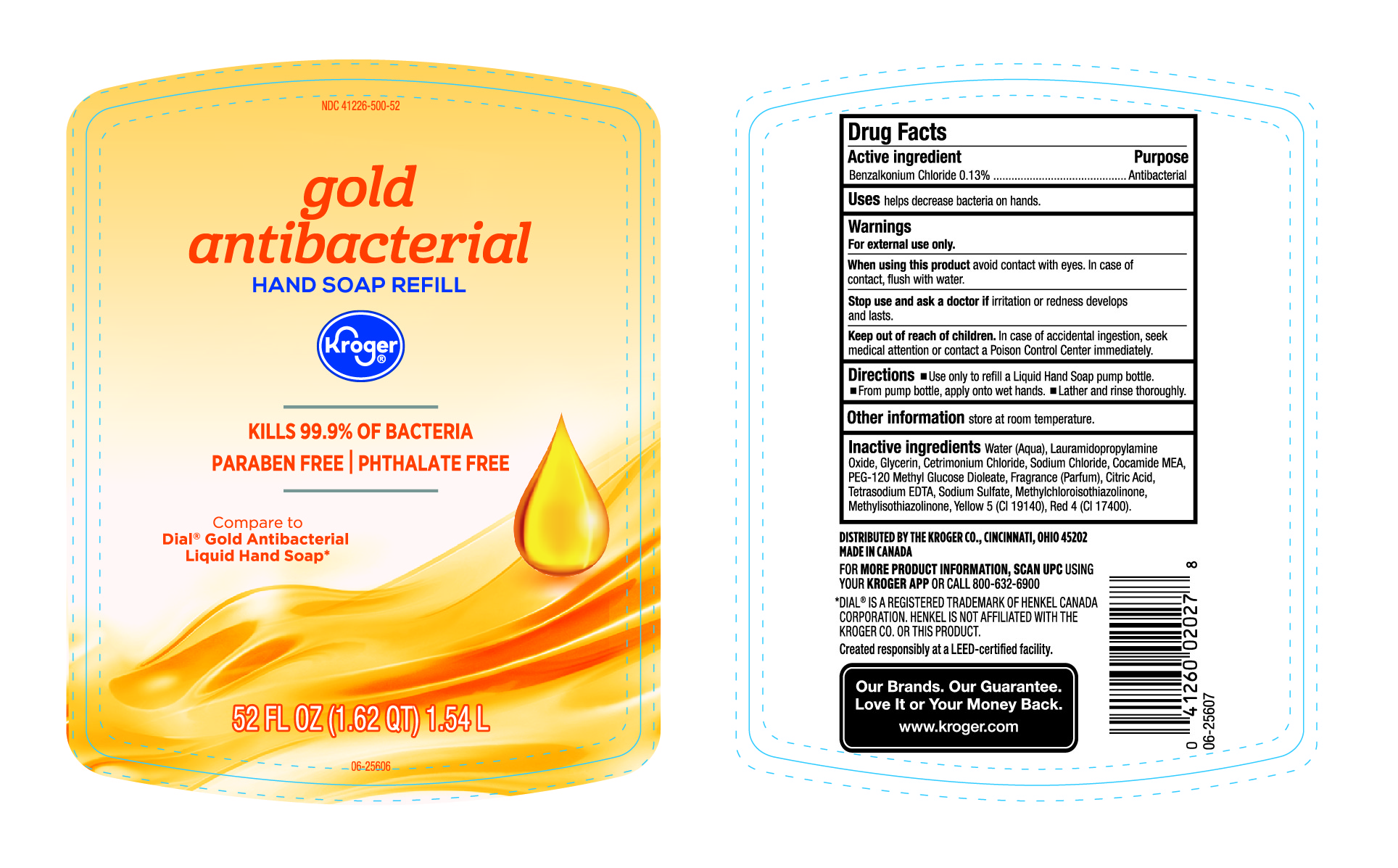 DRUG LABEL: Kroger Antibacterial
NDC: 41226-500 | Form: LIQUID
Manufacturer: Kroger Company
Category: otc | Type: HUMAN OTC DRUG LABEL
Date: 20240224

ACTIVE INGREDIENTS: BENZALKONIUM CHLORIDE 130 mg/100 mL
INACTIVE INGREDIENTS: COCO MONOETHANOLAMIDE; FD&C YELLOW NO. 5; SODIUM CHLORIDE; GLYCERIN; WATER; CETRIMONIUM CHLORIDE; PEG-120 METHYL GLUCOSE DIOLEATE; SODIUM SULFATE; EDETATE SODIUM; LAURAMIDOPROPYLAMINE OXIDE; CITRIC ACID MONOHYDRATE; FD&C RED NO. 4; METHYLCHLOROISOTHIAZOLINONE; METHYLISOTHIAZOLINONE; FRAGRANCE CLEAN ORC0600327

Kroger Gold Antibacterial Hand Soap

Active Ingredient

Benzalkonium Chloride 0.13%

Purpose

Antibacterial

Uses

Helps decrease bacteria on hands

Warnings

For external use only

When using this product

Avoid contact with eyes. In case of contact, flush with water.

Stop use and ask a doctor if

Irritation or redness develops and lasts.

Keep out of reach of children

In case of accidental ingestion, seek medical attention or contact a Poison Control Center immediately.

Directions

- From Pump bottle, apply onto wet hands
- Lather and rinse thoroughly.

Other Information

Store at room Temperature.

Inactive Ingredients

Water (Aqua), Lauramidopropylamine Oxide, Glycerin, Cetrimonium Chloride, Sodium Chloride, Cocamide MEA, PEG-120 Methyl Glucose Dioleate, Fragrance (Parfum), Citric Acid, Tetrasodium EDTA, Sodium Sulfate, Methylchloroisothiazolinone, Meisothiazolinone, Yellow 5 (CI 19140), Red 4 (CI 17400).